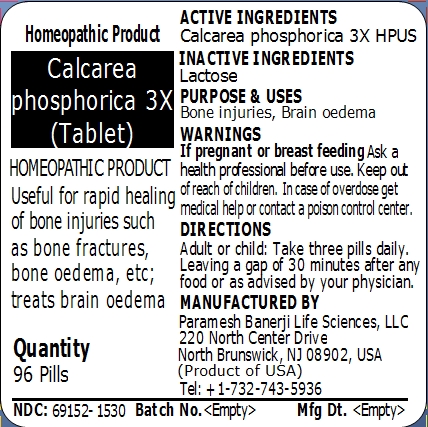 DRUG LABEL: Calcarea phosphorica 3X (Tablet)
NDC: 69152-1530 | Form: PELLET
Manufacturer: Paramesh Banerji Life Sciences LLC
Category: homeopathic | Type: HUMAN OTC DRUG LABEL
Date: 20141218

ACTIVE INGREDIENTS: TRIBASIC CALCIUM PHOSPHATE 3 [hp_X]/1 1
INACTIVE INGREDIENTS: LACTOSE

Principal Display Panel

Homeopathic Product

Calcarea phosphorica 3X (Tablet)

Homeopathic Product

Quantity

96 Pills

Active Ingredients

Calcarea phosphorica 3X HPUS

Inactive Ingredients

Lactose

Purpose

Useful for rapid healing of bone injuries such as bone fractures, bone oedema, etc; treats brain oedema

Uses

Useful for rapid healing of bone injuries such as bone fractures, bone oedema, etc; treats brain oedema

Warnings

If pregnant or breast feeding ask a health professional before use.

Keep out of reach of children. In case of overdose get medical help or contact a poison control center.

Direction

Adult or child: Take three pills daily. Leaving a gap of 30 minutes after any food or as advised by your physician.

Manufactured by

Paramesh Banerji Life Sciences, LLC

220 North Center Drive

North Brunswick, NJ 08902, USA

Product of USA

Tel: +1-732-743-5936